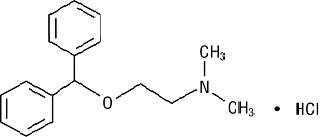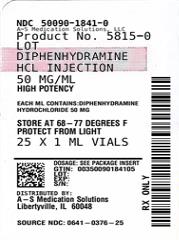 DRUG LABEL: Diphenhydramine Hydrochloride
NDC: 50090-1841 | Form: INJECTION
Manufacturer: A-S Medication Solutions
Category: prescription | Type: HUMAN PRESCRIPTION DRUG LABEL
Date: 20260211

ACTIVE INGREDIENTS: DIPHENHYDRAMINE HCL 50 mg/1 mL
INACTIVE INGREDIENTS: BENZETHONIUM CHLORIDE 100 ug/1 mL; WATER; SODIUM HYDROXIDE; HYDROCHLORIC ACID

Diphenhydramine Hydrochloride Injection, USP
Rx only

DESCRIPTION

Diphenhydramine Hydrochloride Injection is a sterile, nonpyrogenic solution for intravenous or deep intramuscular use as an antihistaminic agent. Each mL contains diphenhydramine hydrochloride 50 mg and benzethonium chloride 100 mcg in Water for Injection. pH 4.0-6.5; sodium hydroxide and/or hydrochloric acid added, if needed, for pH adjustment.

The chemical name of diphenhydramine hydrochloride is 2-(Diphenylmethoxy)-N,N-dimethylethylamine hydrochloride. The structural formula is as follows:

C17H21NO • HCl MW 291.82

Diphenhydramine hydrochloride occurs as a white crystalline powder and is freely soluble in water and alcohol.

CLINICAL PHARMACOLOGY

Diphenhydramine hydrochloride is an antihistamine with anticholinergic (drying) and sedative side effects. Antihistamines appear to compete with histamine for cell receptor sites on effector cells.

Diphenhydramine hydrochloride in the injectable form has a rapid onset of action. Diphenhydramine is widely distributed throughout the body, including the CNS. A portion of the drug is excreted unchanged in the urine, while the rest is metabolized via the liver. Detailed information on the pharmacokinetics of Diphenhydramine Hydrochloride Injection is not available.

INDICATIONS AND USAGE

Diphenhydramine Hydrochloride Injection is effective in adults and pediatric patients, other than premature infants and neonates, for the following conditions when the oral form is impractical:

Antihistaminic

For amelioration of allergic reactions to blood or plasma, in anaphylaxis as an adjunct to epinephrine and other standard measures after the acute symptoms have been controlled and for other uncomplicated allergic conditions of the immediate type when oral therapy is impossible or contraindicated.

Motion Sickness

For active treatment of motion sickness.

Antiparkinsonism

For use in parkinsonism, when oral therapy is impossible or contraindicated, as follows: parkinsonism in the elderly who are unable to tolerate more potent agents, mild cases of parkinsonism in other age groups and in other cases of parkinsonism in combination with centrally acting anticholinergic agents.

CONTRAINDICATIONS

Use in Neonates or Premature Infants

This drug should not be used in neonates or premature infants.

Use in Nursing Mothers

Because of the higher risk of antihistamines for infants generally, and for neonates and prematures in particular, antihistamine therapy is contraindicated in nursing mothers.

Use as a Local Anesthetic

Because of the risk of local necrosis, this drug should not be used as a local anesthetic.

Antihistamines are also Contraindicated in the Following Conditions

Hypersensitivity to diphenhydramine hydrochloride and other antihistamines of similar chemical structure.

WARNINGS

Antihistamines should be used with considerable caution in patients with narrow-angle glaucoma, stenosing peptic ulcer, pyloroduodenal obstruction, symptomatic prostatic hypertrophy or bladder-neck obstruction.

Local necrosis has been associated with the use of subcutaneous or intradermal use of intravenous diphenhydramine.

Use in Pediatric Patients

In pediatric patients, especially, antihistamines in overdosage may cause hallucinations, convulsions or death.

As in adults, antihistamines may diminish mental alertness in pediatric patients. In the young pediatric patient, particularly, they may produce excitation.

Use in the Elderly (approximately 60 years or older)

Antihistamines are more likely to cause dizziness, sedation and hypotension in elderly patients.

PRECAUTIONS

General

Diphenhydramine hydrochloride has an atropine-like action and, therefore, should be used with caution in patients with a history of bronchial asthma, increased intraocular pressure, hyperthyroidism, cardiovascular disease or hypertension. Use with caution in patients with lower respiratory disease, including asthma.

Information for Patients

Patients taking diphenhydramine hydrochloride should be advised that this drug may cause drowsiness and has an additive effect with alcohol.

Patients should be warned about engaging in activities requiring mental alertness, such as driving a car or operating appliances, machinery, etc.

Drug Interactions

Diphenhydramine hydrochloride has additive effects with alcohol and other CNS depressants (hypnotics, sedatives, tranquilizers, etc.)

MAO inhibitors prolong and intensify the anticholinergic (drying) effects of antihistamines.

Carcinogenesis, Mutagenesis, Impairment of Fertility

Long-term studies in animals to determine mutagenic and carcinogenic potential have not been performed.

Pregnancy

Teratogenic Effects—Pregnancy Category B

Reproduction studies have been performed in rats and rabbits at doses up to 5 times the human dose and have revealed no evidence of impaired fertility or harm to the fetus due to diphenhydramine hydrochloride. There are, however, no adequate and well-controlled studies in pregnant women. Because animal reproduction studies are not always predictive of human response, this drug should be used during pregnancy only if clearly needed.

Pediatric Use

Diphenhydramine should not be used in neonates and premature infants (see CONTRAINDICATIONS).

Diphenhydramine may diminish mental alertness, or in the young pediatric patient, cause excitation. Overdosage may cause hallucinations, convulsions or death (see WARNINGS and OVERDOSAGE).

See also DOSAGE AND ADMINISTRATION section.

ADVERSE REACTIONS

The most frequent adverse reactions are italicized.

General

Urticaria; drug rash; anaphylactic shock; photosensitivity; excessive perspiration; chills; dryness of mouth, nose and throat.

Cardiovascular System

Hypotension, headache, palpitations, tachycardia, extrasystoles.

Hematologic System

Hemolytic anemia, thrombocytopenia, agranulocytosis.

Nervous System

Sedation, sleepiness, dizziness, disturbed coordination, fatigue, confusion, restlessness, excitation, nervousness, tremor, irritability, insomnia, euphoria, paresthesia, blurred vision, diplopia, vertigo, tinnitus, acute labyrinthitis, neuritis, convulsions.

Gastrointestinal System

Epigastric distress, anorexia, nausea, vomiting, diarrhea, constipation.

Genitourinary System

Urinary frequency, difficult urination, urinary retention, early menses.

Respiratory System

Thickening of bronchial secretions, tightness of chest and wheezing, nasal stuffiness.

OVERDOSAGE

Antihistamine overdosage reactions may vary from central nervous system depression to stimulation. Stimulation is particularly likely in pediatric patients. Atropine-like signs and symptoms, dry mouth; fixed, dilated pupils; flushing, and gastrointestinal symptoms may also occur.

Stimulants should not be used.

Vasopressors may be used to treat hypotension.

DOSAGE AND ADMINISTRATION

THIS PRODUCT IS FOR INTRAVENOUS OR INTRAMUSCULAR ADMINISTRATION ONLY.

Diphenhydramine Hydrochloride Injection is indicated when the oral form is impractical.

DOSAGE SHOULD BE INDIVIDUALIZED ACCORDING TO THE NEEDS AND THE RESPONSE OF THE PATIENT.

Pediatric Patients, Other Than Premature Infants and Neonates

5 mg/kg/24 hours or 150 mg/m^2/24 hours. Maximum daily dosage is 300 mg. Divide into four doses, administered intravenously at a rate generally not exceeding 25 mg/min, or deep intramuscularly.

Adults

10 to 50 mg intravenously at a rate generally not exceeding 25 mg/min, or deep intramuscularly; 100 mg if required; maximum daily dosage is 400 mg.

Parenteral drug products should be inspected visually for particulate matter and discoloration prior to administration, whenever solution and container permit.

HOW SUPPLIED

Product: 50090-1841

NDC: 50090-1841-0 1 mL in a VIAL / 25 in a PACKAGE